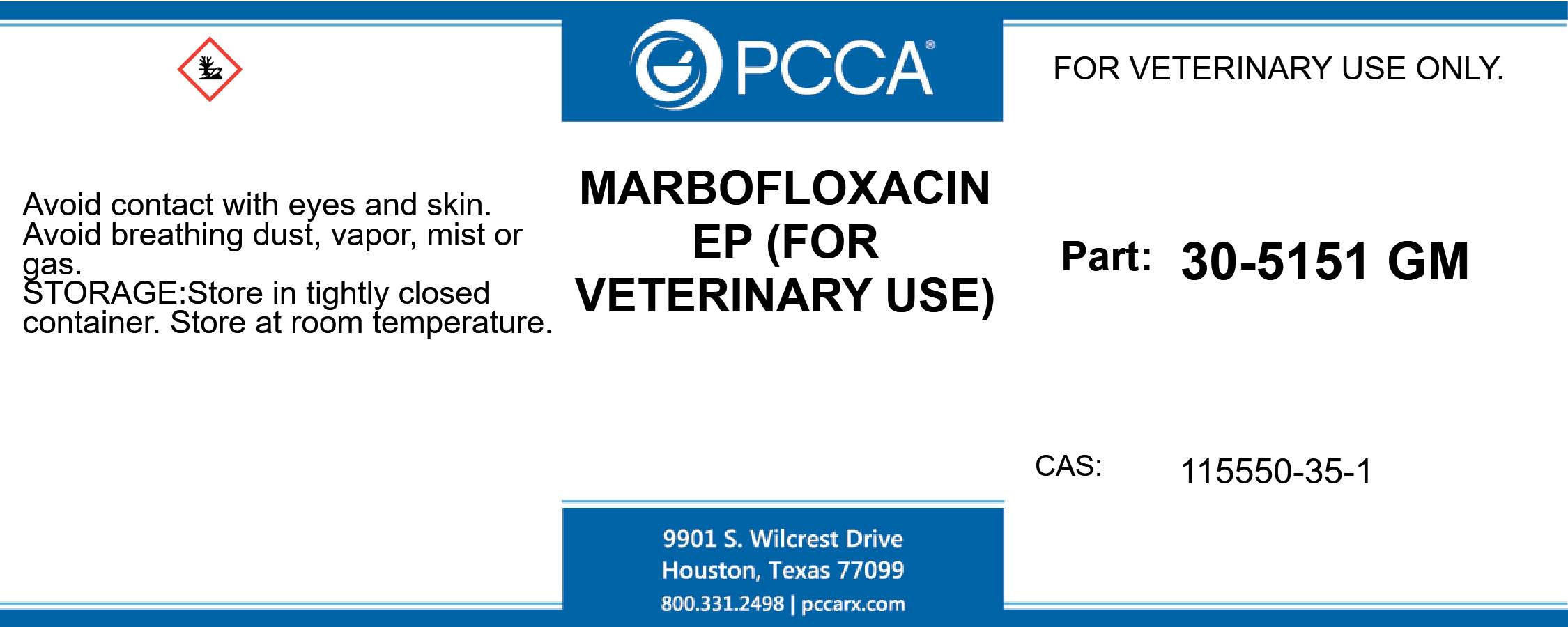 DRUG LABEL: MARBOFLOXACIN
NDC: 51927-5151 | Form: POWDER
Manufacturer: Professional Compounding Centers of America
Category: other | Type: BULK INGREDIENT
Date: 20210916

ACTIVE INGREDIENTS: MARBOFLOXACIN 1 kg/1 kg

30-5151 MARBOFLOXACIN EP 51927-5151-00

MARBOFLOXACIN EP (FOR VETERINARY USE) FOR VETERINARY USE ONLY. PART: 30-5151 GM CAS: 115550-35-1 AVOID CONTACT WITH EYES AND SKIN. AVOID BREATHING DUST, VAPOR, MIST OR GAS. STORE IN TIGHTLY CLOSED CONTAINER. STORE AT ROOM TEMPERATURE.

MARBOFLOXACIN EP (FOR VETERINARY USE)

FOR VETERINARY USE ONLY.

PART: 30-5151 GM

CAS: 115550-35-1

AVOID CONTACT WITH EYES AND SKIN. AVOID BREATHING DUST, VAPOR, MIST OR GAS. STORE IN TIGHTLY CLOSED CONTAINER. STORE AT ROOM TEMPERATURE.